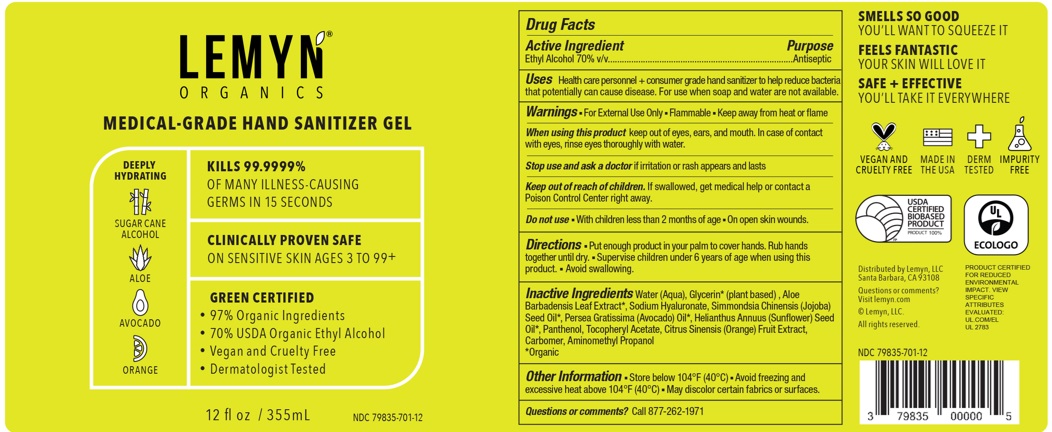 DRUG LABEL: Lemyn Organics Medical-Grade Hand Sanitizer
NDC: 79835-701 | Form: GEL
Manufacturer: Lemyn LLC
Category: otc | Type: HUMAN OTC DRUG LABEL
Date: 20251010

ACTIVE INGREDIENTS: ALCOHOL 70 mL/100 mL
INACTIVE INGREDIENTS: HYALURONATE SODIUM; JOJOBA OIL; .ALPHA.-TOCOPHEROL ACETATE; ORANGE; AMINOMETHYLPROPANOL; GLYCERIN; ALOE VERA LEAF; WATER; CARBOMER HOMOPOLYMER, UNSPECIFIED TYPE; SUNFLOWER OIL; PANTHENOL; AVOCADO OIL

Lemyn Organics Medical-Grade Hand Sanitizer Gel

Active Ingredient

Ethyl Alcohol 70% v/v

Purpose

Antiseptic

Uses

Health care personnel + consumer grade hand sanitizer to help reduce bacteria that potentially can cause disease. For use when soap and water are not available.

Warnings

- For External Use Only
- Flammable
- Keep away from heat or flame

When using this product

keep out of eyes, ears, and mouth. In case of contact with eyes, rinse eyes thoroughly with water.

Stop use and ask a doctor

if irritation or rash appears and lasts

Keep out of reach of children.

If swallowed, get medical help or contact a Poison Control Center right away.

Do not use

- With children less than 2 months of age
- On open skin wounds

Directions

- Put enough product in your palm to cover hands. Rub hands together until dry.
- Supervise children under 6 years of age when using this product.
- Avoid swallowing.

Inactive Ingredients

Water (Aqua), Glycerin* (plant based), Aloe Barbadensis Leaf Extract*, Sodium Hyaluronate, Simmondsia Chinensis (Jojoba) Seed Oil*, Persea Gratissima (Avocado) Oil*, Helianthus Annuus (Sunflower) Seed Oil*, Panthenol, Tocopheryl Acetate, Citrus Sinensis (Orange) Fruit Extract, Carbomer, Aminomethyl Propanol

*Organic

Other Information

- Store below 104F (40C)
- Avoid freezing and excessive heat above 104F (40C)
- May discolor certain fabrics or sufaces.

Questions or comments?

Call 877-262-1971

Company Information

Distributed by Lemyn, LLC

Santa Barbara, CA 93108

Questions or comments?

Visit lemyn.com